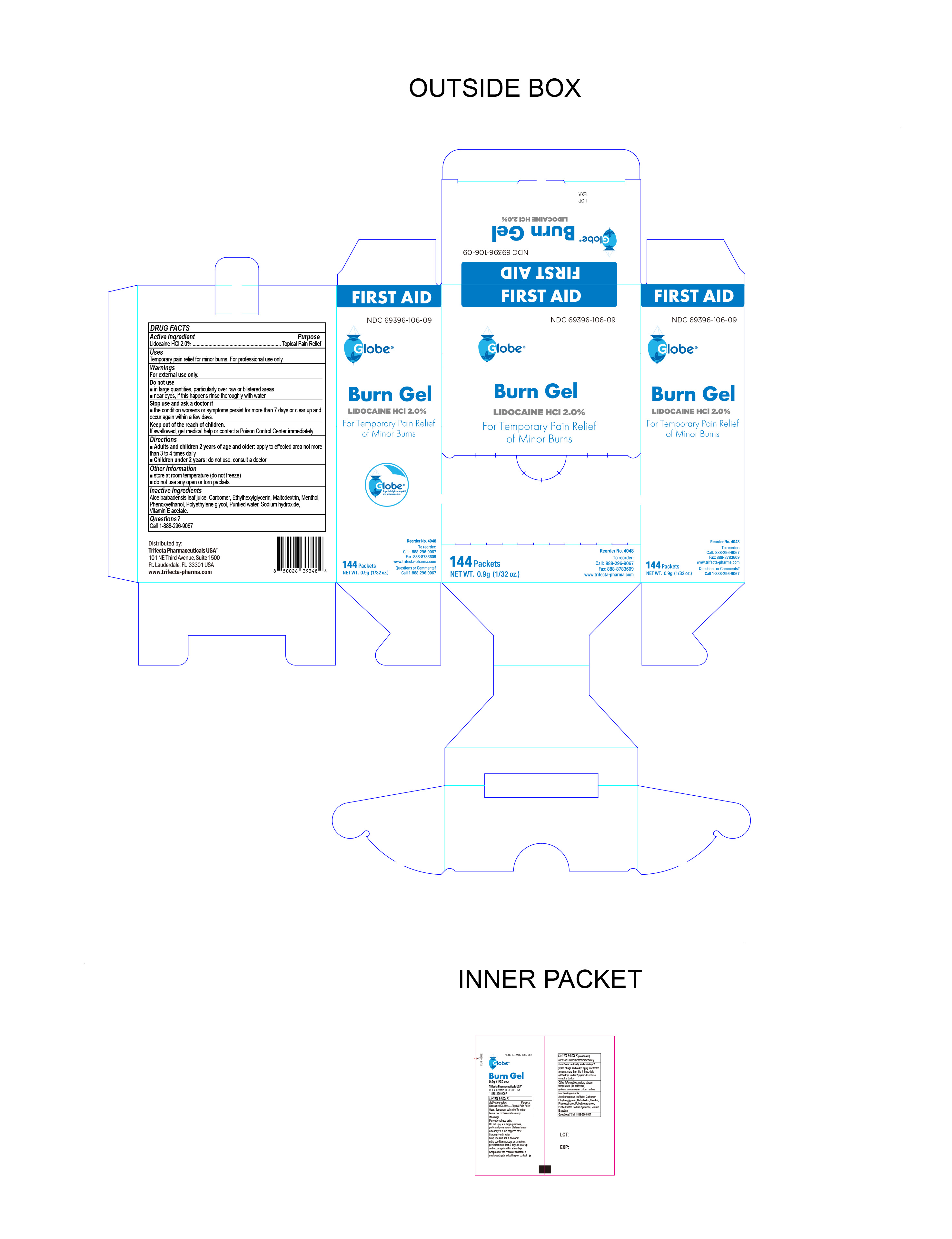 DRUG LABEL: Burn Gel
NDC: 69396-106 | Form: GEL
Manufacturer: Trifecta Pharmaceuticals USA LLC
Category: otc | Type: HUMAN OTC DRUG LABEL
Date: 20240712

ACTIVE INGREDIENTS: LIDOCAINE HYDROCHLORIDE 0.02 g/1 g
INACTIVE INGREDIENTS: .ALPHA.-TOCOPHEROL; CARBOMER HOMOPOLYMER, UNSPECIFIED TYPE; MENTHOL; WATER; ETHYLHEXYLGLYCERIN; PROPYLENE GLYCOL; ALOE VERA LEAF; SODIUM HYDROXIDE; MALTODEXTRIN; PHENOXYETHANOL

Globe First Aid Burn Gel

Active Ingredient

Lidocaine HCL 2%

Purpose

Topical Pain Relief

Uses

Temporary pain relief for minor burns. For professional use only.

Warnings

For external Use Only

Do not use

- in large quantities, particularly over raw or blistered areas
- near eyes, if this happens rinse thoroughly with water

Directions

Adults and children 2 years of age and older: apply to affected area not more than 3 to 4 times daily.

Children under 2 years: do not use, consult a doctor

Inactive Ingredients

Aloe barbadensis leaf juice, Carbomer, Ethylhexylglycerin, Maltodextrin, Menthol, Phenoxyethanol, Propylene glycol, purified water, Triethanolamine, Vitamin E acetate

Questions?

Call 1-888-296-9067

Stop Use and Ask a doctor if

The condition worsens or symptoms persist for more than 7 days or clear up and occur again within a few days.

Storage Information

- Store at room temperature (do not freeze)
- do not use any opened or torn packets

Keep out of reach of children

If swallowed, get medical help or contact a Poison Control Center immediately.

Other Information

Distributed By:

Trifecta Pharmaceuticals USA®

101 NE Third Ave. Ste 1500

Ft. Lauderdale, FL. 33301 USA

www.trifecta-pharma.com